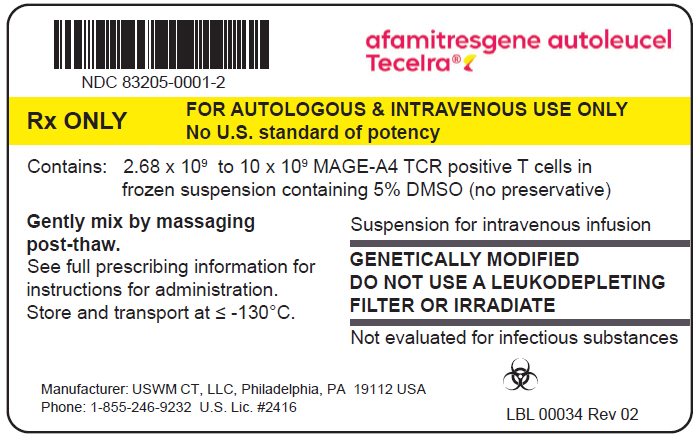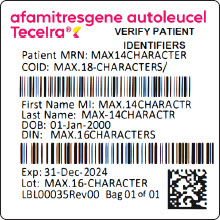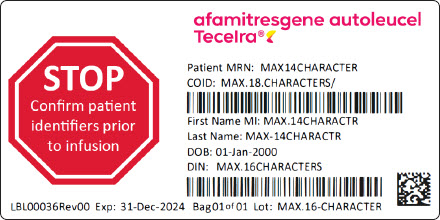 DRUG LABEL: TECELRA
NDC: 83205-0001 | Form: INJECTION, SUSPENSION
Manufacturer: USWM, LLC
Category: other | Type: CELLULAR THERAPY
Date: 20260122

ACTIVE INGREDIENTS: AFAMITRESGENE AUTOLEUCEL 10000000000 1/1 1
INACTIVE INGREDIENTS: DIMETHYL SULFOXIDE

HIGHLIGHTS OF PRESCRIBING INFORMATION

These highlights do not include all the information needed to use TECELRA safely and effectively. See full prescribing information for TECELRA.
TECELRA® (afamitresgene autoleucel) suspension, for intravenous infusion
Initial U.S. Approval: 2024

WARNING: CYTOKINE RELEASE SYNDROME

See full prescribing information for complete boxed warning.

Cytokine Release Syndrome (CRS), which may be severe or life-threatening, occurred in patients receiving TECELRA. At the first sign of CRS, immediately evaluate patient for hospitalization and institute treatment with supportive care. Ensure that healthcare providers administering TECELRA have immediate access to medications and resuscitative equipment to manage CRS (2.2, 5.1).

1 INDICATIONS AND USAGE

TECELRA is a melanoma-associated antigen A4 (MAGE-A4)-directed genetically modified autologous T cell immunotherapy indicated for the treatment of adults with unresectable or metastatic synovial sarcoma who have received prior chemotherapy, are HLA-A*02:01P, -A*02:02P, -A*02:03P, or -A*02:06P positive and whose tumor expresses the MAGE-A4 antigen as determined by FDA-approved or cleared companion diagnostic devices.

This indication is approved under accelerated approval based on overall response rate and duration of response (14). Continued approval for this indication may be contingent upon verification and description of clinical benefit in a confirmatory trial.

2 DOSAGE AND ADMINISTRATION

For autologous use only. For intravenous use only.
Prior to infusion

- Verify patient's identity prior to infusion (2.2).
- Administer a lymphodepleting regimen of cyclophosphamide and fludarabine (2.2).
- Premedicate with acetaminophen and an H1-antihistamine (2.2).

TECELRA Dose and Administration
The recommended dose is between 2.68 x 10^9 to 10 x 10^9 MAGE-A4 T cell receptor (TCR) positive T cells (2.1).

Administer each infusion bag within one hour of thawing.

DO NOT USE a leukodepleting filter (2.2).
DO NOT USE prophylactic systemic corticosteroids (2.2).

3 DOSAGE FORMS AND STRENGTHS

TECELRA is

- A cell suspension for intravenous infusion.
- Provided in one or more infusion bag(s) containing 2.68 x 10^9 to 10 x 10^9 MAGE-A4 TCR positive T cells (3).

4 CONTRAINDICATIONS

DO NOT use TECELRA in adults who are heterozygous or homozygous for HLA-A*02:05P (4).

5 WARNINGS AND PRECAUTIONS

Immune Effector Cell-Associated Neurotoxicity Syndrome (ICANS): Monitor for ICANS events for at least 4 weeks after treatment with TECELRA (5.2).

Prolonged Severe Cytopenia: Patients may exhibit severe cytopenia (hemoglobin < 8.0 g/dL, neutrophils < 1,000/mm^3, platelets < 50,000/mm^3) for several weeks following lymphodepleting chemotherapy and TECELRA infusion. Monitor blood counts prior to and after TECELRA infusion (5.3).

Infections: Monitor patients for signs and symptoms of infection; treat appropriately (5.4).

Secondary Malignancies: In the event that a secondary malignancy occurs after treatment with TECELRA, contact 1-855-246-9232 (5.5).

Hypersensitivity Reactions: Monitor for hypersensitivity reactions during infusion (5.6).

Effects on Ability to Drive and Use Machines: Advise patients to refrain from driving and engaging in hazardous occupations or activities, such as operating heavy or potentially dangerous machinery, for at least 4 weeks after receiving TECELRA (5.2).

6 ADVERSE REACTIONS

Most common adverse reactions (≥ 20%) were, cytokine release syndrome, nausea, vomiting, fatigue, infections, pyrexia, constipation, dyspnea, abdominal pain, non-cardiac chest pain, decreased appetite, tachycardia, back pain, hypotension, diarrhea, and edema.

Grade 3 or 4 laboratory abnormalities (≥20%) were lymphocyte count decreased, neutrophil count decreased, white cell blood count decreased, red blood cell decreased, and platelet count decreased (6.1).

The most common serious adverse reactions (≥ 5%) were cytokine release syndrome and pleural effusion (6.1).

To report SUSPECTED ADVERSE REACTIONS, contact USWM CT, LLC at 1-855-246-9232 or FDA at 1-800-FDA-1088 or www.fda.gov/medwatch.

FULL PRESCRIBING INFORMATION

WARNING: CYTOKINE RELEASE SYNDROME

Cytokine Release Syndrome (CRS), which may be severe or life-threatening, occurred in patients receiving TECELRA. At the first sign of CRS, immediately evaluate patient for hospitalization and institute treatment with supportive care. Ensure that healthcare providers administering TECELRA have immediate access to medications and resuscitative equipment to manage CRS [see Preparation and Administration (2.2), and Warnings and Precautions (5.1)].

1 INDICATIONS AND USAGE

TECELRA is a melanoma-associated antigen A4-(MAGE-A4)-directed genetically modified autologous T cell immunotherapy indicated for the treatment of adults with unresectable or metastatic synovial sarcoma who have received prior chemotherapy, are HLA-A*02:01P, -A*02:02P, -A*02:03P, or -A*02:06P positive and whose tumor expresses the MAGE-A4 antigen as determined by FDA-approved or cleared companion diagnostic devices.

This indication is approved under accelerated approval based on overall response rate and durability of response [see Clinical Studies (14)]. Continued approval for this indication may be contingent upon verification and description of clinical benefit in a confirmatory trial.

2 DOSAGE AND ADMINISTRATION

For autologous use only. For intravenous use only.

2.1 Recommended Dose

The recommended dose is between 2.68 x 10^9 to 10 x 10^9 MAGE-A4 T cell receptor (TCR) positive T cells administered as a single intravenous infusion.

TECELRA is provided as a single dose for infusion in one or more infusion bag(s). Verify the number of bags received for the indicated dose prior to preparation for infusion.

2.2 Preparation and Administration

Receipt of TECELRA

Plan for TECELRA to arrive prior to beginning lymphodepleting chemotherapy.

Ensure storage conditions in vapor phase of liquid nitrogen (≤ -130°C).

TECELRA is shipped directly to the healthcare facility in the vapor phase of a liquid nitrogen shipper. Upon receipt of TECELRA confirm the patient's identifiers on the metal cassette and product bag.

Inspect the product for obvious signs of damage and contact 1-855-246-9232 if any anomalies are identified at the time of receipt.

Transfer TECELRA in the original packaging, containing the cassette(s) protecting the infusion bag(s), to onsite storage at ≤ -130°C before the shipper expires.

Store TECELRA in a manner that is consistent with How Supplied/Storage and Handling (16). If unforeseen circumstances prevent proper storage of TECELRA consistent with How Supplied/Storage and Handling (16), contact 1-855-246-9232 to arrange for return shipment.

Preparing Patient for TECELRA Administration

Confirm availability of TECELRA at the healthcare facility prior to starting the lymphodepleting chemotherapy regimen.

Match the patient's identity with the patient identifiers on the TECELRA cassette(s) and infusion bag(s). Do not infuse TECELRA if the information on the patient-specific label(s) does not match the intended patient.

Administer a lymphodepleting chemotherapy regimen of fludarabine 30 mg/m^2/day intravenously for 4 days starting on the seventh day before TECELRA infusion (Day-7 to Day -4) and cyclophosphamide 600 mg/m^2/day intravenously for 3 days starting the seventh day before TECELRA infusion (Day -7 to Day -5).

Refer to fludarabine prescribing for information on fludarabine dosage in patients with renal impairment.

Short-acting or pegylated granulocyte-colony stimulating factor (G-CSF) may be administered at the discretion of the physician, and according with institutional standards, from 24 hours after last day of lymphodepleting chemotherapy (from Day -3) until resolution of neutropenia.

Premedication

Premedicate with an H1-antihistamine and acetaminophen according to institutional standard practice, approximately 30-60 minutes prior to TECELRA infusion.

Avoid prophylactic systemic corticosteroids, as it may interfere with the activity of TECELRA.

Preparation of TECELRA for Administration

Do not thaw the product until it is ready to be used. Coordinate the timing of TECELRA thaw and infusion. Confirm infusion time in advance and adjust the start time of TECELRA thaw such that it will be available for infusion when the patient is ready.

A TECELRA dose may be contained in one or more infusion bag(s). Verify the number of bags received for the indicated dose prior to preparation of TECELRA for infusion. If more than one bag will be infused for the treatment dose, thaw and administer the contents of each infusion bag completely before proceeding to thaw and infuse the contents of the next infusion bag.

1. Confirm patient identity. Prior to TECELRA preparation, match the patient's identity with the patient identifiers on each TECELRA cassette. Do not remove the TECELRA infusion bag(s) from the cassette(s) if the information on the patient-specific label does not match the patient's identity. Contact 1-855-246-9232 if there are any discrepancies between the labels and the patient identifiers.

2. Once patient identity is confirmed, remove TECELRA infusion bag(s) from the cassette(s) and check that the patient identifiers on the cassette label match the patient identifiers on the bag label. Contact 1-855-246-9232 if there are any discrepancies between the patient identifiers on the cassette and bag labels.

3. Inspect the infusion bag for any breaches of container integrity such as breaks or cracks before thawing. If the bag is compromised, do not infuse the contents and call 1-855-246-9232.

4. Place the infusion bag inside a second sealable, preferably sterile bag per institutional standard practice.

5. Thaw the infusion bag at approximately 37°C using a water bath or dry thaw method, until there is no visible ice in the infusion bag.

6. Gently mix the contents of the bag by massaging, to disperse visible cell clumps. Small clumps of cellular material should disperse with gentle manual massaging. Do not infuse TECELRA if clumps are not dispersed. Call 1-855-246-9232.

7. Keep TECELRA at ambient temperature (20°C to 25°C) once thawed. Do not pre-filter into a different container, wash, spin down, or resuspend TECELRA in new media prior to infusion.

8. Administer within one hour.

TECELRA Administration

9. Do not use a leukodepleting filter.

10. Follow universal precautions and local biosafety guidelines for handling and disposal of TECELRA to avoid potential transmission of infectious diseases, due to the presence of human blood cells that are genetically modified with replication incompetent, self-inactivating lentiviral vector.

11. Confirm patient identity with the patient identifiers on the infusion bag(s). Do not infuse TECELRA if the information on the patient-specific label does not match the intended patient. Call 1-855-246-9232. Prime the tubing of the infusion set with 0.9% sodium chloride solution prior to infusion.

12. Administer the TECELRA infusion bag via intravenous infusion within one hour. Administer the entire contents of the TECELRA infusion bag.

13. After the entire contents of the TECELRA infusion bag are infused, rinse the infusion bag with approximately 50mL 0.9% sodium chloride solution to ensure all product is delivered.

14. If more than one infusion bag has been received, administer the content of each infusion bag completely before proceeding to thaw and infuse the content of the next infusion bag, following steps 1-14 for all subsequent infusion bags.

3 DOSAGE FORMS AND STRENGTHS

TECELRA is a cell suspension for intravenous infusion. A single dose of TECELRA contains 2.68 x 10^9 to 10 x 10^9 MAGE-A4 TCR positive T cells in one or more infusion bag(s) [see How Supplied/Storage and Handling (16)].

4 CONTRAINDICATIONS

DO NOT use TECELRA in adults who are heterozygous or homozygous for HLA- A*02:05P.

5 WARNINGS AND PRECAUTIONS

5.1 Cytokine Release Syndrome

Cytokine release syndrome (CRS), including potentially life-threatening reaction has been observed following administration of TECELRA. CRS occurred in 75% of patients, 2% of whom had Grade ≥ 3 CRS. The median time to onset was 2 days (range: 1 to 5 days) and the median time to resolution was 3 days (range: 1 to 14 days). The most common symptoms were fever (97%), tachycardia (52%), hypotension (30%), nausea/vomiting (21%) and headache (15%) [see Adverse Reactions (6)]. Management for CRS (including Grade 1) was tocilizumab (55%). Thirteen patients received one dose and five patients received more than one dose. Of the five patients who received more than one dose of tocilizumab, two patients received dexamethasone in addition to tocilizumab.

Ensure that healthcare providers administering TECELRA have immediate access to medications and resuscitative equipment to manage CRS. Ensure patients are euvolemic prior to initiating the infusions.

During and following TECELRA administration, closely monitor patients for signs and symptoms of CRS. Following treatment with TECELRA, monitor patients for at least 7 days at the healthcare facility for CRS. Continue to monitor patients for CRS for at least 4 weeks following treatment with TECELRA. Counsel patients to seek medical attention should signs or symptoms of CRS occur. At the first sign of CRS, immediately evaluate patient for hospitalization and institute treatment with supportive care based on severity and consider further management per current practice guidelines.

5.2 Immune Effector Cell-associated Neurotoxicity Syndrome

Immune Effector Cell-associated Neurotoxicity Syndrome (ICANS) has been observed following administration of TECELRA. One patient (2%) had Grade 1 ICANS. Time to onset was two days and time to resolution was one day. Symptoms included mild mental status changes. Other symptoms may include disorientation to time and place, mild drowsiness, mild inattention. Severe symptoms may include altered level of consciousness, seizures, cerebral edema, impairment of cognitive skills, progressive aphasia, motor weakness.

Ensure that healthcare providers administering TECELRA have immediate access to medications and resuscitative equipment to manage ICANS.

During and following TECELRA administration, closely monitor patients for signs and symptoms of ICANS. Following treatment with TECELRA, monitor patients for at least 7 days at the healthcare facility for ICANS. Continue to monitor patients for ICANS for at least 4 weeks following treatment with TECELRA. Counsel patients to seek medical attention should signs or symptoms of ICANS occur. At the first sign of ICANS, immediately evaluate patients for hospitalization and institute treatment with supportive care based on severity and consider further management per current practice guidelines.

Effect on Ability to Drive and Use Machines

Due to the potential for neurologic events, including dizziness and presyncope, patients receiving TECELRA are at risk for altered or decreased coordination in the 4 weeks following infusion.

Advise patients to refrain from driving and engaging in hazardous occupations or activities, such as operating heavy or potentially dangerous machinery, during this initial period.

5.3 Prolonged Severe Cytopenia

Patients may exhibit severe cytopenias, including neutropenia and thrombocytopenia [see Adverse Reactions (6)].

Patients exhibited anemia, neutropenia, and/or thrombocytopenia for several weeks following lymphodepleting chemotherapy and TECELRA infusion. Patients with Grade ≥ 3 cytopenia not resolved by week 4 included anemia (9%), neutropenia (11%), and thrombocytopenia (5%). The median time to resolution was 7.3 weeks (range: 6.1 to 8.4 weeks) for anemia, 9.3 weeks (range: 6.4 to 12.3 weeks) for neutropenia and 6.3 weeks (range: 6.1 to 6.4 weeks) for thrombocytopenia.

Monitor blood counts after TECELRA infusion. Manage cytopenia with growth factor and blood product transfusion according to local institutional guidelines/clinical practice.

5.4 Infections

Infections may occur following lymphodepleting chemotherapy and TECELRA infusion. Infections (all grades) occurred in 32% of patients with synovial sarcoma. Grade 3 or higher infections occurred in 14% of patients.

Do not administer TECELRA to patients with active infections and/or inflammatory disorders.

Monitor patients for signs and symptoms of infection before and after TECELRA infusion and treat patients appropriately.

Febrile neutropenia was observed in patients after TECELRA infusion and may be concurrent with CRS. In the event of febrile neutropenia, evaluate for infection and manage with broad-spectrum antibiotics, fluids and other supportive care, as medically indicated.

Viral reactivation has occurred in patients following treatment with TECELRA. Perform screening for Epstein-Barr Virus, Cytomegalovirus, Hepatitis B Virus, Hepatitis C Virus, Human Immunodeficiency Virus, and any other infectious agents if clinically indicated. Consider antiviral therapy to prevent viral reactivation per local guidelines.

5.5 Secondary Malignancies

Patients treated with TECELRA may develop secondary malignancies or recurrence of their cancer. Monitor for secondary malignancies.

In the event that a secondary malignancy occurs, contact 1-855-246-9232 to obtain instructions on patient samples to collect for testing.

5.6 Hypersensitivity Reactions

Serious hypersensitivity reactions, including anaphylaxis, may occur due to dimethyl sulfoxide (DMSO) in TECELRA. Observe patients for hypersensitivity reactions during infusion.

5.7 Potential for HIV Nucleic Acid Test False-Positive Results

The lentiviral vector used to make TECELRA has limited, short spans of genetic material which are identical to HIV. Therefore, some commercial HIV nucleic acid tests may yield false-positive results in patients who have received TECELRA.

6 ADVERSE REACTIONS

6.1 Clinical Trials Experience

Because clinical trials are conducted under widely varying conditions, adverse reaction rates observed in the clinical trials of a drug cannot be directly compared to rates in the clinical trials of another drug and may not reflect the rates observed in practice.

The safety data described in this section reflects the exposure to TECELRA in 44 patients with advanced synovial sarcoma treated in the SPEARHEAD-1 clinical trial (Cohort 1). Patients with synovial sarcoma received TECELRA across a dose of 2.68 x 10^9 to 10 x 10^9 MAGE-A4 TCR positive T cells [see Clinical Studies (14)].

Serious adverse reactions occurred in 52% of patients with synovial sarcoma. The most common serious adverse reactions (occurring in ≥ 5%) included CRS (9%) and pleural effusion (7%).

Table 1 summarizes adverse reactions that occurred in at least 10% of patients.

Table 1. Adverse Reactions Occurring in ≥10% of Patients in SPEARHEAD-1 (Cohort 1)
SOC Grouped Term | (N=44)
SOC Grouped Term | All Grades n (%) | Grade ≥ 3 n (%)
Investigations
Weight decreased | 5 (11) | 1 (2)
Gastrointestinal disorders
Nausea | 29 (66) | 1 (2)
Vomiting | 16 (36) | 0 (0)
Constipation | 14 (32) | 0 (0)
Abdominal pain | 11 (25) | 2 (5)
Diarrhea | 9 (21) | 0 (0)
General disorders and administration site conditions
Fatigue | 15 (34) | 0 (0)
Pyrexia | 14 (32) | 2 (5)
Non-cardiac chest pain | 10 (23) | 1 (2)
Chills | 7 (16) | 0 (0)
Edema | 9 (21) | 0 (0)
Asthenia | 7 (16) | 1 (2)
Chest pain | 6 (14) | 0 (0)
Immune system disorders
Cytokine Release Syndrome [As per American Society for Transplantation and Cellular Therapy (ASTCT) criteria^1] | 33 (75) | 1 (2)
Infections and infestations
Any infection [Any infection includes all infection terms under the 'Infections and infestations' System Organ Class] | 14 (32) | 6 (14)
Nervous system disorders
Headache | 8 (18) | 1 (2)
Dizziness | 5 (11) | 0 (0)
Metabolism and nutrition disorders
Decreased appetite | 10 (23) | 1 (2)
Musculoskeletal and connective tissue disorders
Back pain | 9 (21) | 2 (5)
Pain in extremity | 6 (14) | 0 (0)
Respiratory, thoracic, and mediastinal disorders
Dyspnea | 11 (25) | 2 (5)
Cough | 8 (18) | 0 (0)
Vascular disorders
Hypotension | 9 (21) | 0 (0)
Hypertension | 7 (16) | 1 (2)
Cardiac disorders
Sinus Tachycardia/ Tachycardia | 9 (21) | 0 (0)
Skin and subcutaneous tissue disorders
Alopecia | 6 (14) | 0 (0)

Other clinically important adverse reactions occurring in patients receiving TECELRA include Grade 1 ICANS reported in one patient (2%).

Table 2. Laboratory Abnormalities [Abnormalities are laboratory values that were considered an adverse event] Worsened from Baseline in ≥10% of Patients in SPEARHEAD-1 (Cohort 1)
Laboratory Abnormalities | N=44
Laboratory Abnormalities | All Grades n (%) | Grade 3 or 4 n (%)
Lymphocyte count decreased | 43 (98) | 43 (98)
Neutrophil count decreased | 42 (96) | 40 (91)
White blood cell decreased | 42 (96) | 38 (86)
Red blood cell decreased | 42 (96) | 14 (32)
Platelet count decreased | 36 (82) | 9 (21)
Alanine aminotransferase increased | 20 (46) | 2 (5)
Grading based on NCI CTCAE version 5.0.

7 DRUG INTERACTIONS

None

8 USE IN SPECIFIC POPULATIONS

8.1 Pregnancy

Risk Summary

There are no available data with TECELRA use in pregnant women. No animal reproductive and developmental toxicity studies have been conducted with TECELRA to assess whether it can cause fetal harm when administered to a pregnant woman. It is not known if TECELRA has the potential to be transferred to the fetus and cause fetal toxicity. Therefore, TECELRA is not recommended for women who are pregnant, and pregnancy after TECELRA administration should be discussed with the treating physician. Report all pregnancies following treatment with TECELRA to 1-855-246-9232.

In the U.S. general population, the estimated background risk of major birth defects and miscarriage in clinically recognized pregnancies is 2-4% and 15-20%, respectively.

8.2 Lactation

Risk Summary

There is no information regarding the presence of TECELRA in human milk, the effect on the breastfed infant, and the effects on milk production. The developmental and health benefits of breastfeeding should be considered along with the mother's clinical need for TECELRA and any potential adverse effects on the breastfed infant from TECELRA or from the underlying maternal condition.

8.3 Females and Males of Reproductive Potential

Pregnancy Testing

Verify pregnancy status of females with reproductive potential prior to starting treatment with TECELRA.

Contraception

There are insufficient exposure data to provide a recommendation concerning duration of contraception following treatment with TECELRA.

8.4 Pediatric Use

The safety and effectiveness of TECELRA have not been established in pediatric patients.

8.5 Geriatric Use

Of the 44 patients with synovial sarcoma in the SPEARHEAD-1 study that received TECELRA, 6.8% were 65 years of age or older. Clinical studies of TECELRA did not include sufficient numbers of patients aged 65 and over to conclude whether they respond differently from younger patients.

11 DESCRIPTION

TECELRA (afamitresgene autoleucel) is a melanoma-associated antigen A4 (MAGE- A4)-directed genetically modified autologous T cell immunotherapy product consisting of CD4 and CD8 positive T cells transduced with a self-inactivating lentiviral vector (LV) expressing an affinity-enhanced T cell receptor (TCR) specific for the human MAGE-A4.

Autologous T cells transduced with MAGE-A4-c1032 LV express the affinity-enhanced TCR on the cell surface. The TCR recognizes an HLA-A*02 restricted MAGE-A4 peptide. MAGE-A4 is an intracellular cancer-testis antigen that has restricted expression in normal tissues and is expressed in synovial sarcoma.

TECELRA is prepared from the patient's peripheral blood mononuclear cells (PBMCs), which are obtained via a standard leukapheresis procedure. The PBMCs are enriched for T cells and are then transduced with a replication-incompetent LV containing the MAGE-A4 TCR transgene. The transduced T cells are expanded, washed, formulated into a suspension, and cryopreserved. The product must pass a sterility test before release and shipping as a frozen suspension in one or more infusion bag(s). The product is thawed prior to infusion back into the patient [see Preparation and Administration (2.2), How Supplied/Storage and Handling (16)].

The drug product formulation contains 5% dimethyl sulfoxide (DMSO).

12 CLINICAL PHARMACOLOGY

12.1 Mechanism of Action

TECELRA is a genetically modified autologous T cell immunotherapy consisting of CD4 and CD8 positive T cells transduced with a self-inactivating LV to express an affinity- enhanced TCR specific for human MAGE-A4 on the cell surface.

The TCR recognizes an HLA-A*02 restricted MAGE-A4 peptide. MAGE-A4 is an intracellular cancer-testis antigen that has restricted expression in normal tissues and is expressed in synovial sarcoma. Antigen-specific activation of TECELRA via TCR- peptide-HLA-A*02 complex results in T cell proliferation, cytokine secretion, and killing of MAGE-A4/HLA-A*02 expressing synovial sarcoma cells.

12.2 Pharmacodynamics

In patients with synovial sarcoma who were treated with TECELRA, serum concentrations of cytokines and other soluble factors involved in cellular homeostasis, T cell activation, and inflammation (e.g. IFNγ, IL-6, IL-8, IL-15, and IL-2Rα) increased post-infusion, peaking between Days 3-8.

12.3 Pharmacokinetics

TECELRA exhibited an initial engraftment and expansion phase followed by contraction, and then persistence. High inter-individual variability was observed.

The pharmacokinetics of TECELRA in patients with synovial sarcoma are summarized in Table 3.

Table 3. Pharmacokinetics of Afamitresgene Autoleucel in SPEARHEAD-1 (Cohort 1) [All patients received a dose within the range of 2.68 x 10^9 to 10 x 10^9 MAGE-A4 TCR positive T cells.]
PK Parameter | N | Statistics | Value
tmax (day) | 44 | Median (range) | 7 (1-89)
Cmax (DNA copies/μg) | 44 | Geometric mean (CV%) | 189269 (109.1%)
AUC0-7D (day*DNA copies/μg) | 44 | Geometric mean (CV%) | 729653 (110.8%)
AUC0-28D (day*DNA copies/μg) | 41 | Geometric mean (CV%) | 3074205 (164.7%)
AUC0-3M (day*DNA copies/μg) | 35 | Geometric mean (CV%) | 4988965 (242.7%)
AUC0-6M (day*DNA copies/μg) | 33 | Geometric mean (CV%) | 6784047 (313.4%)

Specific Populations

The pharmacokinetics of afamitresgene autoleucel (Cmax, AUC0-7D, AUC0-28D, AUC0-3M, AUC0-6M) were not impacted by body weight, body mass index, sex, age (range: 19 to 76 years), and baseline tumor sum of longest diameter (SLD).

Hepatic and renal impairment studies of TECELRA were not conducted.

13 NONCLINICAL TOXICOLOGY

13.1 Carcinogenesis, Mutagenesis, Impairment of Fertility

No carcinogenicity or genotoxicity studies have been conducted with TECELRA.

A genomic insertion site analysis was performed on TECELRA products from five patients. There was no evidence for preferential integration near genes of concern. No studies have been conducted to evaluate the effects of TECELRA on fertility.

14 CLINICAL STUDIES

Locally Inoperable/ Metastatic Synovial Sarcoma

The efficacy of TECELRA was evaluated in a multicenter, single-arm, open-label clinical trial (SPEARHEAD-1, Cohort 1). The study enrolled HLA-A*02:01P, HLA-A*02:02P, HLA-A*02:03P, and HLA-A*02:06P allele positive patients with inoperable or metastatic synovial sarcoma who had received prior systemic therapy with either doxorubicin and/or ifosfamide and whose tumor expressed the MAGE-A4 tumor antigen. The study included patients with measurable disease according to RECIST v1.1, Eastern Cooperative Oncology Group (ECOG) performance status of 0 or 1, and glomerular filtration rate (GFR) ≥ 60 mL/min. The study excluded patients with HLA-A*02:05P in either allele, patients on systemic corticosteroids for at least 14 days prior to leukapheresis and lymphodepletion, and recipients of allogeneic hematopoietic stem cell transplants.

Patients underwent high resolution HLA typing at a centralized testing site and had tumor samples tested for MAGE-A4 expression by an immunohistochemistry (IHC) clinical trial assay at a centralized testing site. Patients underwent leukapheresis for collection of autologous cells for processing and manufacture into TECELRA. Risk of manufacturing or delivery failure was 8% in the clinical trial (4/52) patients.

Patients received lymphodepleting chemotherapy with fludarabine 30 mg/m^2/day for 4 days (Day -7 to Day -4) and cyclophosphamide 600mg/ m^2/day for 3 days (Day -7 to Day -5). Patients with GFR 60-79 mL/min received an adjusted fludarabine dose of 20 mg/m^2/day. TECELRA was administered as a single intravenous (IV) infusion on Day 1.

Fifty-two (52) patients were enrolled and underwent leukapheresis, eight of whom did not receive TECELRA due to the following: death (n=3), loss of eligibility prior to lymphodepleting chemotherapy (n=3), withdrawal by patient (n=1), investigator decision (n=1). Forty-five (45) patients with synovial sarcoma received lymphodepletion and one patient withdrew consent before receiving TECELRA. There were 44 patients with synovial sarcoma who received a single infusion of TECELRA.

Among the efficacy analysis population demographic characteristics were as follows: median age was 41 years (range: 19 to 73 years), 50% were female, and 89% were White, and 96% were HLA-A*02:01P.

The median number of prior lines of systemic therapies was three (range: 1 to 12 lines). Prior therapies included ifosfamide (100%), doxorubicin (95%), pazopanib (48%), trabectedin (25%), dacarbazine (11%), and gemcitabine (11%). Between leukapheresis and initiation of lymphodepletion, 16 (36%) of the 44 patients received bridging therapy. The most commonly used bridging therapy was pazopanib (69%). The median dose of TECELRA was 8x10^9 MAGE-A4 TCR positive T cells (range: 2.68 x 10^9 to 9.99 x10^9).

The major efficacy outcome measure was overall response rate (ORR) according to RECISTv1.1 evaluated by independent review committee (IRC). Duration of response (DOR) was an additional outcome measure.The ORR results are presented in Table 4.

Table 4. Efficacy Results [Efficacy assessment was by independent review committee according to Response Evaluation Criteria In Solid Tumors (RECIST) v1.1.] for SPEARHEAD-1 (Cohort 1)
Endpoint | TECELRA Treated Population N=44
Overall Response Rate (95% CI) [Two-sided 95% confidence interval based on exact Clopper-Pearson (exact Binomial) method.] Complete response rate, n (%) Partial response rate, n (%) | 43.2% (28.4, 59.0) 2 (4.5%) 17 (38.6%)
Median Duration of Response [Duration of response only applies to patients with a complete or partial response.] in months (95% CI) [Two-sided 95% confidence interval and % of patients with response duration ≥6 and ≥12 months based on Kaplan-Meier method.] Min, Max Patients with DoR ≥ 6 months, % Patients with DoR ≥ 12 months, % | 6.0 (4.6, NR) 1.9, 36.1+ 45.6% 39.0%
CI= confidence interval; NR= not reached.

The median time to response from TECELRA treatment was 4.9 weeks (95% CI: 4.4 weeks, 8 weeks) by Kaplan Meier estimation.

15 REFERENCES

1. Lee DW, Santomasso BD, Locke FL, et al. ASTCT consensus grading for cytokine release syndrome and neurologic toxicity associated with immune effector cells. Biol Blood Marrow Transplant 2019; 25: 625-638.

16 HOW SUPPLIED/STORAGE AND HANDLING

TECELRA is supplied in one or more infusion bag(s) containing a frozen suspension of genetically modified autologous T cells in 5% DMSO. Each TECELRA infusion bag is individually packed in a metal cassette. Product and patient-specific labels are located on both the product infusion bag(s) and the protective shipping cassette(s).

Each infusion bag (250ml) is contained within a protective metal cassette (NDC 83205-0001-2).

TECELRA is shipped in a liquid nitrogen dry vapor shipper at less than or equal to -130°C.

Store TECELRA in the original packaging, containing the cassette(s) protecting the infusion bag(s), in the vapor phase of liquid nitrogen at less than or equal to -130°C.

17 PATIENT COUNSELING INFORMATION

Advise the patient to read the FDA-approved patient labeling (Medication Guide).

Discuss the following with the patient:

- Inform patients that there is a chance of manufacturing or delivery failure (approximately 8% in the clinical trial). Therefore, a second manufacture of TECELRA may be attempted.
- Inform patients that additional therapy (other than lymphodepletion) may be necessary before TECELRA manufacturing is completed. This may increase the risk of adverse reactions during the pre-infusion period, which could delay or prevent administration of TECELRA.
- Inform patients that following infusion, it will be necessary to be monitored daily at the healthcare facility for at least 7 days for signs and symptoms of cytokine release syndrome (CRS). Patients must remain within proximity of a healthcare facility for at least 4 weeks following infusion.
- Advise patients to seek immediate medical attention if any of the following occur:
  - Cytokine Release Syndrome: inform patients that symptoms may include fever, rigors, fast heartbeat, irregular heartbeat, low blood pressure, lightheadedness or dizziness, shortness of breath, nausea/vomiting, diarrhea, and headache [see Warnings and Precautions (5.1) and Adverse Reactions (6)].
  - Immune Effector Cell-Associated Neurotoxicity Syndrome (ICANS): inform patients that symptoms may include confusion, depressed level of consciousness, delirium, seizures, language difficulty [see Warnings and Precautions (5.2) and Adverse Reactions (6)].
  - Bone marrow suppression and prolonged severe cytopenias: inform patients that symptoms may include bleeding or bruising, tiredness, shortness of breath, fever, pain, redness for several weeks following lymphodepleting chemotherapy and TECELRA blood counts before and after TECELRA infusion should be periodically monitored [see Warnings and Precautions (5.3) and Adverse Reactions (6)].
  - Infections: inform patients that they may exhibit signs or symptoms associated with infection, and that past infections can be reactivated following treatment with TECELRA [see Warnings and Precautions (5.4) and Adverse Reactions (6)].

Advise patients for the need to:

- Contact 1-855-246-9232 if they are diagnosed with a secondary malignancy [see Warnings and Precautions (5.5)].
- Refrain from driving or operating heavy or potentially dangerous machines for at least 4 weeks after TECELRA administration [see Warnings and Precautions (5.2)].

Manufactured by: USWM CT, LLC
351 Rouse Boulevard
Philadelphia, PA 19112
U.S. License Number 2416

© 2026 USWM CT, LLC.

Medication Guide
TECELRA® (pronounced tuh-sel-ruh)
(afamitresgene autoleucel)

Read this Medication Guide before you start your TECELRA treatment. Talk with your healthcare provider if you have questions about your health condition or treatment. Reading this Medication Guide does not take the place of talking with your healthcare provider about your treatment.

What is the most important information I should know about TECELRA?
You will likely be in a hospital before and after getting TECELRA.
TECELRA may cause side effects that can be severe or life-threatening. Call your healthcare provider or get emergency help right away if you get any of the following:
Fever (100.4°F/38°C or higher)
Chills/Shivering
Difficulty breathing
Fast or irregular heartbeat
Low blood pressure
Fatigue
Severe nausea, vomiting, or diarrhea
Severe headache
New skin rash
Tell all your healthcare providers that you were treated with TECELRA.

What is TECELRA?
TECELRA is a medicine, called a genetically modified autologous T cell immunotherapy, that is used to treat synovial sarcoma. It is used when other kinds of treatment do not work.
TECELRA is different from other cancer medicines because it is made from your own white blood cells that are made to recognize and attack your cancer cells.
Your healthcare provider will perform tests to see if TECELRA is right for you.
Before you get TECELRA, tell your healthcare provider about all your medical problems, including:
Seizure, stroke, confusion, or memory loss
Heart, liver or kidney problems
Low blood pressure
Lung or breathing problems
Recent or active infection
Past infections which can be reactivated following treatment with TECELRA
Low blood counts
Pregnancy, you think you may be pregnant, or plan to become pregnant
Breastfeeding
Taking a blood thinner
Tell your healthcare provider about all the medicines you take, including prescription and over-the-counter medicines, vitamins, and herbal supplements.

How will I get TECELRA?
Since TECELRA is made from your own white blood cells, your blood will be collected by a process called "leukapheresis" (loo-kah-fur-ee-sis). This gets sent to a company to make the TECELRA for you.
It takes about 6 weeks to get your TECELRA back, but the time may vary.
While your TECELRA is being made, your healthcare provider may give you other medicines to stabilize your cancer.
Before you get your TECELRA, you will get 4 days of chemotherapy to prepare your body.
When your TECELRA is ready, you get a tube (intravenous catheter) placed into your vein and your dose of TECELRA will be given in one or more infusion bags. The infusion may take up to 60 minutes for each infusion bag.
After getting TECELRA, you will be monitored daily at the healthcare facility, for at least 7 days after the infusion.
You should plan to stay close to a healthcare facility for at least 4 weeks. Your healthcare provider will check to see that your treatment is working and help you with any side effects that may occur.
Your healthcare provider will do blood tests to follow your progress. It is important that you have your blood tested. If you miss a scheduled appointment for your collection of blood, call your healthcare provider as soon as possible to reschedule.

What are the possible or reasonably likely side effects of TECELRA?
The most common side effects of TECELRA include:
Nausea
Vomiting
Fatigue
Constipation
Fever (100.4°F/38°C or higher)
Infection
Abdominal pain
Difficulty breathing
Decreased appetite
Diarrhea
Low blood pressure
Back pain
Fast heart rate
Chest pain
General body swelling
Low white blood cells
Low red blood cells
Low platelets
What should I avoid after receiving TECELRA?
Do not drive, operate heavy machinery, or do other activities that could be dangerous for at least 4 weeks after you get TECELRA.
Do not donate blood, organs, tissues, or cells for transplantation.

What are the ingredients in TECELRA?
Active ingredient: afamitresgene autoleucel
Inactive ingredients: Dimethyl Sulfoxide (DMSO)

Issued: Aug 2024

PRINCIPAL DISPLAY PANEL - Bag and Cassette Label

afamitresgene autoleucel
Tecelra®

NDC 83205-0001-2

Rx ONLY

FOR AUTOLOGOUS & INTRAVENOUS USE ONLY
No U.S. standard of potency

Contains: 2.68 x 10^9 to 10 x 10^9 MAGE-A4 TCR positive T cells in
frozen suspension containing 5% DMSO (no preservative)

Gently mix by massaging
post-thaw.
See full prescribing information for
instructions for administration.
Store and transport at ≤ -130°C.

Suspension for intravenous infusion
GENETICALLY MODIFIED
DO NOT USE A LEUKODEPLETING
FILTER OR IRRADIATE
Not evaluated for infectious substances

Manufacturer: USWM CT, LLC, Philadelphia, PA 19112 USA
Phone: 1-855-246-9232 U.S. Lic. #2416

LBL 00034 Rev 02

PRINCIPAL DISPLAY PANEL - Bag Label - Patient Identifier

afamitresgene autoleucel
Tecelra®
VERIFY PATIENT
IDENTIFIERS

Patient MRN: MAX14CHARACTER
COID: MAX.18-CHARACTERS/

First Name MI: MAX.14CHARACTR
Last Name: MAX-14CHARACTR
DOB: 01-Jan-2000
DIN: MAX.16CHARACTERS

Exp. 31-Dec-2024
Lot: MAX.16-CHARACTER
LBL 00035 Rev 00 Bag 01 of 01

PRINCIPAL DISPLAY PANEL - Cassette Label - Patient Identifier

STOP
Confirm patient
identifiers prior
to infusion

afamitresgene autoleucel
Tecelra®

Patient MRN: MAX14CHARACTER
COID: MAX.18.CHARACTERS/

First Name MI: MAX.14CHARACTR
Last Name: MAX-14CHARACTR
DOB: 01-Jan-2000
DIN: MAX.16CHARACTERS

LBL 00036 Rev 00 Exp. 31-Dec-2024 Bag 01 of 01 Lot: MAX.16-CHARACTER